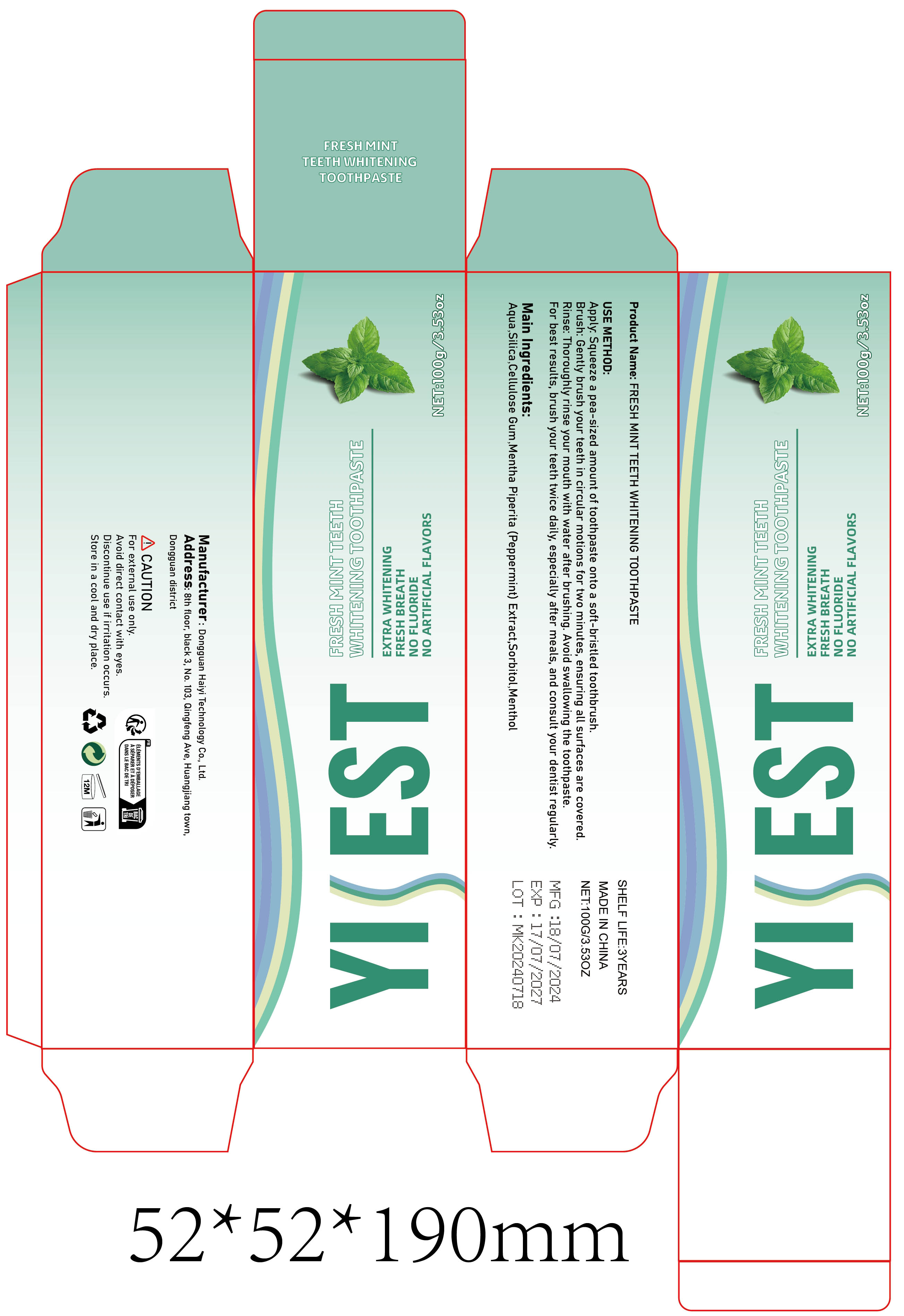 DRUG LABEL: FRESH MINT TEETH WHITENING
NDC: 84732-085 | Form: PASTE
Manufacturer: Dongguan Haiyi Technology Co.,Ltd.
Category: otc | Type: HUMAN OTC DRUG LABEL
Date: 20241105

ACTIVE INGREDIENTS: SILICON DIOXIDE 1 mg/100 g
INACTIVE INGREDIENTS: WATER; SORBITOL; MENTHA PIPERITA (PEPPERMINT) LEAF EXTRACT; CELLULOSE GUM; MENTHOL

Active ingredient

Silica

Inactive ingredient

Aqua.Cellulose Gum.Mentha Piperita (Peppermint) Extract,Sorbitol,Menthol

Purpose section

Freshens breath, whitens and cleanses.

Warning

1).For external use only, avoid directcontact with eyes, lf you feel any
discomfort, stop using itand wash it with plenty of water. In severe cases,
pleaseseek medical attention in time.
2). Not allowed to be used ondamaged skin,

stop use

This product may cause allergic reactions in asmall number of people.
lf youexperience any discomfort,please stop using it immediately.

not use

Not suitable for use by children, pregnantor breast feeding people.

OUT OF CHILDREN

KEEP THE PRODUCT OUT OF REACH OF CHILDREN to

HOW TO USE

Apply Squeeze a pea-sized amount of toothpaste onto a soft-bristled toothbrush.

Brush: Gently brush your teeth in circular motions for two minutes, ensuring all surfaces are covered

Rinse: Thoroughly rinse your mouth with water after brushing. Avoid swallowing the toothpaste.For best results, brush your teeth twice daily, especially after meals, and consult your dentist regularly.

Dosage

For best results, brush your teeth twice daily, especially after meals, and consult your dentist regularly.